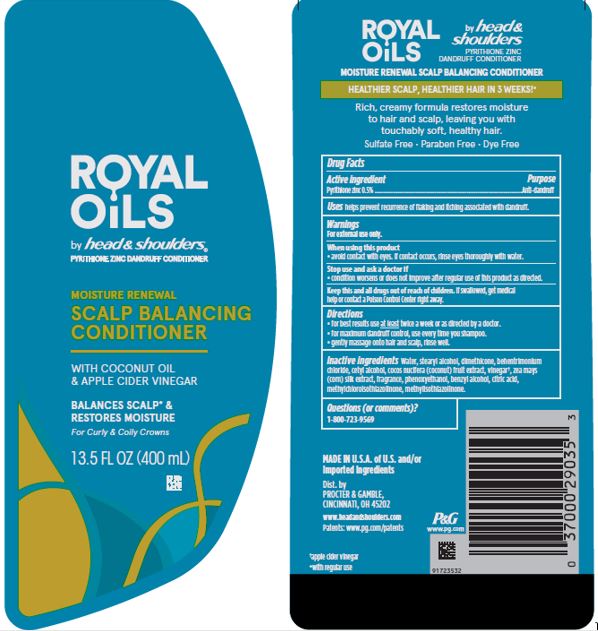 DRUG LABEL: Royal Oils by head and shoulders Moisture Renewal Scalp Balancing Conditioner
NDC: 69423-571 | Form: LOTION
Manufacturer: The Procter & Gamble Manufacturing Company
Category: otc | Type: HUMAN OTC DRUG LABEL
Date: 20251218

ACTIVE INGREDIENTS: PYRITHIONE ZINC 0.5 g/100 mL
INACTIVE INGREDIENTS: APPLE CIDER VINEGAR; CORN SILK; DIMETHICONE; CITRIC ACID MONOHYDRATE; BEHENTRIMONIUM CHLORIDE; WATER; STEARYL ALCOHOL; CETYL ALCOHOL; PHENOXYETHANOL; BENZYL ALCOHOL; COCONUT; METHYLCHLOROISOTHIAZOLINONE; METHYLISOTHIAZOLINONE

Royal Oils by head and shoulders ® Mosisture Renewal Scalp Balancing Conditioner

Drug Facts

Active ingredient

Pyrithione zinc 0.5%

Purpose

Anti-dandruff

Uses

helps prevent recurrence of flaking and itching associated with dandruff.

Warnings

For external use only.

When using this product

- avoid contact with eyes. If contact occurs, rinse eyes thoroughly with water.

Stop use and ask a doctor if

- condition worsens or does not improve after regular use of this product as directed.

KEEP OUT OF REACH OF CHILDREN

Keep this and all drugs out of reach of children. If swallowed, get medical help or contact a Poison Control Center right away.

Directions

- for best results use at least twice a week or as directed by a doctor.
- for maximum dandruff control, use every time you shampoo.
- gently massage into hair and scalp, rinse well.

Inactive ingredients

Water, stearyl alcohol, dimethicone, behentrimonium chloride, cetyl alcohol, cocos nucifera (coconut) fruit extract, vinegar, zea mays (corn) silk extract, fragrance, phenoxyethanol, benzyl alcohol, citric acid, methylchloroisothiazolinone, methylisothiazolinone.

Questions (or comments)?

1-800-723-9569

Dist. by PROCTER & GAMBLE,
CINCINNATI, OH 45202

PRINCIPAL DISPLAY PANEL - 400 mL Bottle Label

ROYAL OILS

by head & shoulders®
pyrithione zinc dandruff conditioner

MOISTURE RENEWAL

SCALP BALANCING

CONDITIONER

ROYAL OILS

WITH COCONUT OIL

& APPLE CIDER VINEGAR

13.5 FL OZ
(400 mL)